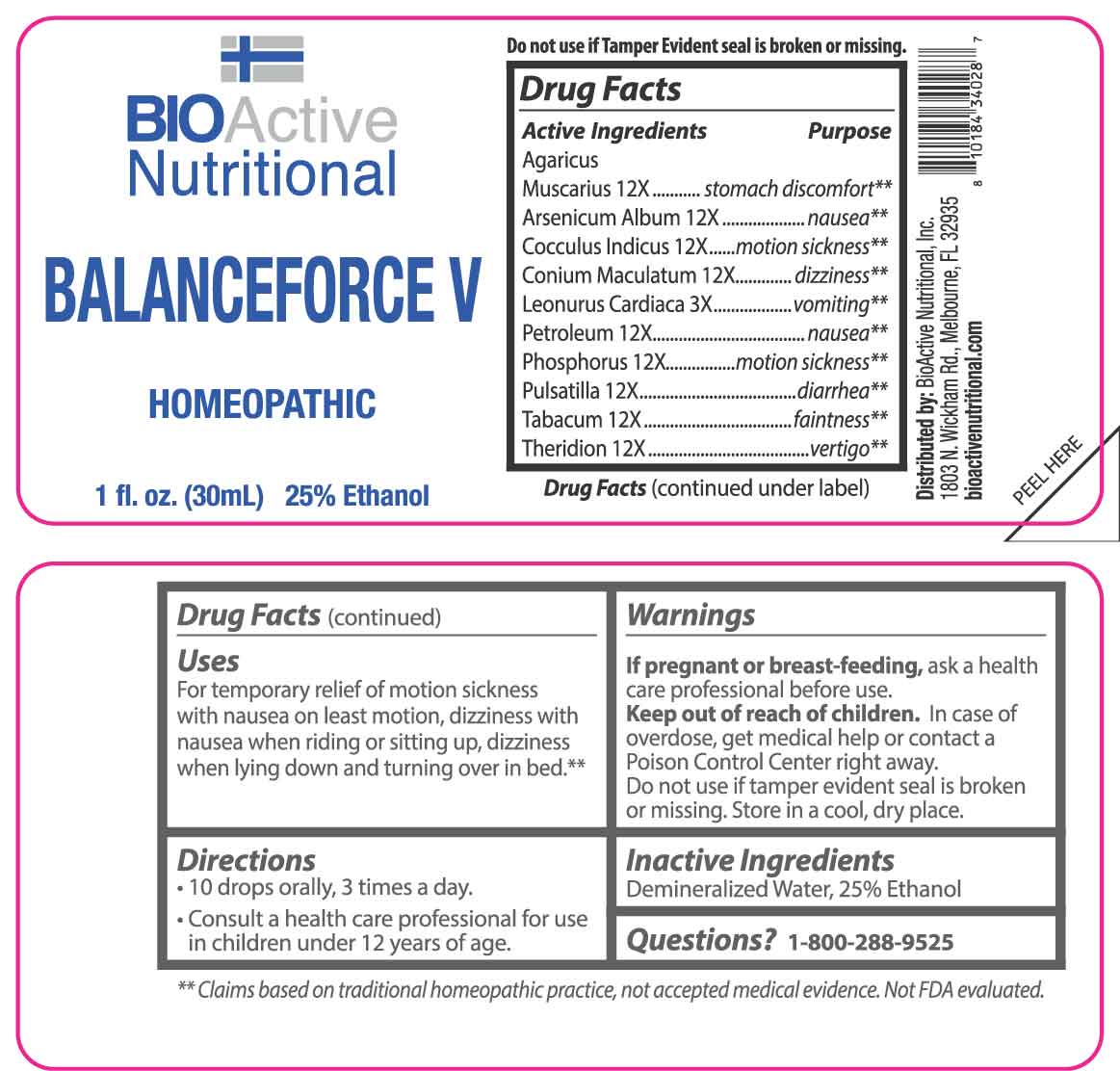 DRUG LABEL: Balanceforce V
NDC: 43857-0592 | Form: LIQUID
Manufacturer: BioActive Nutritional, Inc.
Category: homeopathic | Type: HUMAN OTC DRUG LABEL
Date: 20250602

ACTIVE INGREDIENTS: LEONURUS CARDIACA WHOLE 3 [hp_X]/1 mL; AMANITA MUSCARIA FRUITING BODY 12 [hp_X]/1 mL; ARSENIC TRIOXIDE 12 [hp_X]/1 mL; ANAMIRTA COCCULUS SEED 12 [hp_X]/1 mL; CONIUM MACULATUM FLOWERING TOP 12 [hp_X]/1 mL; KEROSENE 12 [hp_X]/1 mL; PHOSPHORUS 12 [hp_X]/1 mL; PULSATILLA VULGARIS WHOLE 12 [hp_X]/1 mL; TOBACCO LEAF 12 [hp_X]/1 mL; THERIDION CURASSAVICUM 12 [hp_X]/1 mL
INACTIVE INGREDIENTS: WATER; ALCOHOL

DRUG FACTS:

ACTIVE INGREDIENTS:

Agaricus Muscarius 12X, Arsenicum Album 12X, Cocculus Indicus 12X, Conium Maculatum 12X, Leonurus Cardiaca 3X, Petroleum 12X, Phosphorus 12X, Pulsatilla 12X, Tabacum 12X, Theridion 12X.

PURPOSE:

Agaricus Muscarius – stomach discomfort,** Arsenicum Album - nausea,** Cocculus Indicus – motion sickness,** Conium Maculatum - dizziness,** Leonurus Cardiaca - vomiting,** Petroleum - nausea,** Phosphorus – motion sickness,** Pulsatilla - diarrhea,** Tabacum - faintness,** Theridion – vertigo**

**Claims based on traditional homeopathic practice, not accepted medical evidence. Not FDA evaluated.

USES:

For temporary relief of motion sickness with nausea on least motion, dizziness with nausea when riding or sitting up, dizziness when lying down and turning over in bed.

**Claims based on traditional homeopathic practice, not accepted medical evidence. Not FDA evaluated.

WARNINGS:

If pregnant or breast-feeding, ask a health care professional before use.

Keep out of reach of children. In case of overdose, get medical help or contact a Poison Control Center right away.

Do not use if tamper evident seal is broken or missing.

Store in a cool, dry place.

KEEP OUT OF REACH OF CHILDREN:

In case of overdose, get medical help or contact a Poison Control Center right away.

DIRECTIONS:

• 10 drops orally, 3 times a day.

• Consult a health care professional for use in children under 12 years of age.

INACTIVE INGREDIENTS:

Demineralized Water, 25% Ethanol

QUESTIONS:

Distributed by:
BioActive Nutritional, Inc.
1803 N. Wickham Rd.
Melbourne, FL 32935
bioactivenutritional.com

1-800-288-9525

PACKAGE LABEL DISPLAY:

BIOActive Nutritional

BALANCEFORCE V

HOMEOPATHIC

1 FL OZ (30 ml)